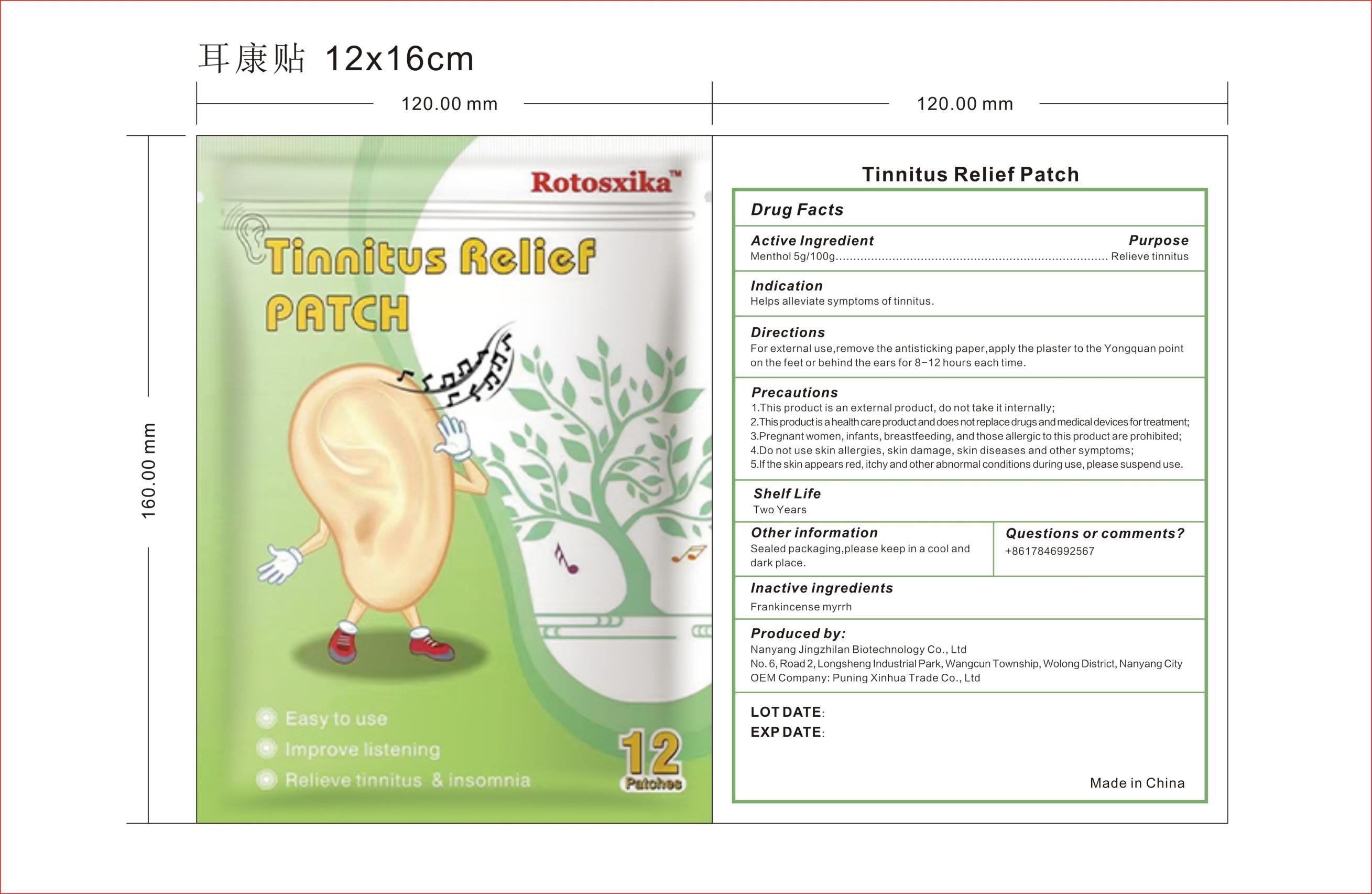 DRUG LABEL: Rotosxika Tinnitus Relief Patch
NDC: 83702-018 | Form: PATCH
Manufacturer: Puning Xinhua Trade Co., Ltd.
Category: otc | Type: HUMAN OTC DRUG LABEL
Date: 20231019

ACTIVE INGREDIENTS: MENTHOL 5 g/100 g
INACTIVE INGREDIENTS: FRANKINCENSE; MYRRH

Tinnitus Relief Patch-83702-018-12

Active ingredient: Menthol 5g/100g

Purpose: Relieve tinnitus

INDICATIONS AND USAGE

Indication:

Helps alleviate symptoms of tinnitus.

Directions:

For external use,remove the antisticking paper,apply the plaster to the Yongquan point on the feet or behind the ears for 8-12 hours each time.

WARNINGS

Precautions

1.This product is an external product, do not take it internally;

2.This product is a health careproduct and does not replace drugs and medical devices for treatment;

3.Pregnant women, infants, breastfeeding, and those allergic to this product are prohibited;

4.Do not use skin allergies, skin damage, skin diseases and other symptoms;

5.If the skin appears red, itchy and other abnormal conditions during use, please suspend use.

Questions or comments? +8617846992567

Inactive Ingredients: Frankincense myrrh.

Other information:

Sealed packaging, please keep in a cool and dark place.

Produced by:
Nanyang Jingzhilan Biotechnology Co.,Ltd
No.6,Road 2,Longsheng Industrial Park,Wangcun Township, Wolong District,Nanyang City
OEM Company: Puning Xinhua Trade Co.,Ltd

Made in China

KEEP OUT OF REACH OF CHILDREN

Same as WARNINGS SECTION

Label